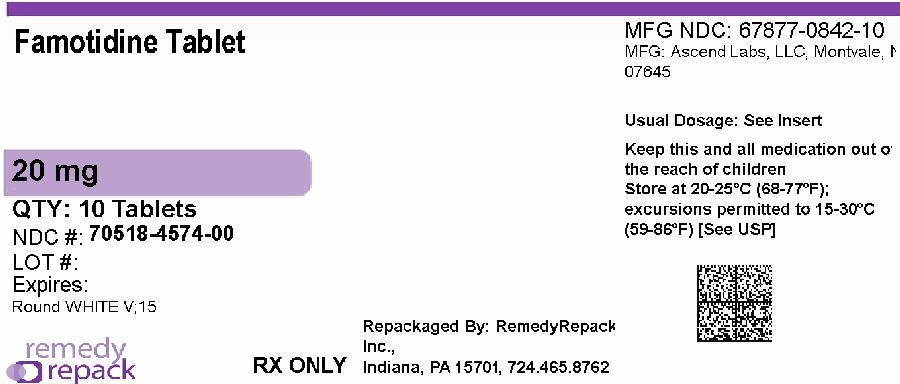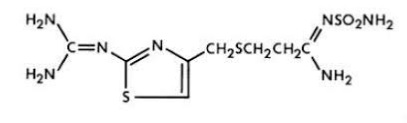 DRUG LABEL: FAMOTIDINE
NDC: 70518-4574 | Form: TABLET, FILM COATED
Manufacturer: REMEDYREPACK INC.
Category: prescription | Type: HUMAN PRESCRIPTION DRUG LABEL
Date: 20260217

ACTIVE INGREDIENTS: FAMOTIDINE 20 mg/1 1
INACTIVE INGREDIENTS: HYDROXYPROPYL CELLULOSE, UNSPECIFIED; MAGNESIUM STEARATE; MICROCRYSTALLINE CELLULOSE; SODIUM STARCH GLYCOLATE TYPE A; TITANIUM DIOXIDE; TRIACETIN; POLYETHYLENE GLYCOL, UNSPECIFIED; STARCH, CORN; HYPROMELLOSE, UNSPECIFIED

HIGHLIGHTS OF PRESCRIBING INFORMATION

These highlights do not include all the information needed to use FAMOTIDINE TABLETS safely and effectively. See full prescribing information for FAMOTIDINE TABLETS.
FAMOTIDINE tablets, for oral use
Initial U.S. Approval: 1986

1 INDICATIONS & USAGE

Famotidine is a histamine-2 (H2) receptor antagonist indicated (1):

In adult and pediatric patients 40 kg and greater for the treatment of:

- active duodenal ulcer (DU).
- active gastric ulcer.
- symptomatic nonerosive gastroesophageal reflux disease (GERD).
- erosive esophagitis due to GERD, diagnosed
  by biopsy.

In adults for the:

- treatment of pathological hypersecretory conditions (e.g., Zollinger-Ellison syndrome, multiple endocrine neoplasias).
- reduction of the risk of DU recurrence.

2 DOSAGE & ADMINISTRATION

Indication | Recommended Dosage (2.1)
Adult and Pediatric Patients | 40 kg and greater
Active DU | 40 mg once daily; or 20 mg twice daily
Active Gastric Ulcer | 40 mg once daily
GERD | 20 mg twice daily
Erosive Esophagitis | 20 mg twice daily; or 40 mg twice daily
Adults
Pathological Hypersecretory Conditions | 20 mg every 6 hours; adjust to patient needs; maximum 160 mg every 6 hours
Risk Reduction of DU Recurrence | 20 mg once daily

- See full prescribing information for complete dosing information, including dosing in renal impairment, and recommended treatment duration. (2.1,2.2)

Administration (2.3):

- Take once daily before bedtime or twice daily in the morning and before bedtime with or without food.

3 DOSAGE FORMS & STRENGTHS

Tablets: 20 mg(3)

4 CONTRAINDICATIONS

History of serious hypersensitivity reactions (e.g., anaphylaxis) to famotidine or other H2receptor antagonists. (4)

5 WARNINGS AND PRECAUTIONS

- Central Nervous System (CNS) Adverse Reactions:Elderly patients and patients with renal impairment at increased risk; reduce the dosage. (2.2, 5.1, 8.5, 8.6)
- GI Malignancy:Absence of GI symptoms does not preclude the presence of gastric malignancy; evaluate prior to initiating therapy. (5.2)

6 ADVERSE REACTIONS

The most common adverse reactions are: headache, dizziness, constipation, and diarrhea. (6.1)

To report SUSPECTED ADVERSE REACTIONS, contact Ascend Laboratories, LLC at 1-877-272-7901 or FDA at 1-800-FDA-1088 or www.fda.gov/medwatch.

7 DRUG INTERACTIONS

- Drugs Dependent on Gastric pH for Absorption:Systemic exposure of the concomitant drug may be significantly reduced leading to loss of efficacy. See full prescribing information for a list of interacting drugs. (7.1)
- Tizanidine (CYP1A2) Substrate:Potential for substantial increases in blood concentrations of tizanidine resulting in hypotension, bradycardia or excessive drowsiness; avoid concomitant use, if possible. (7.2)

8 USE IN SPECIFIC POPULATIONS

- Geriatric Use:Use the lowest effective dose for an elderly patient and monitor renal function. (2.2, 5.1, 8.5)
- Renal Impairment:Risk of CNS adverse reactions and QT prolongation in patients with moderate and severe renal impairment; reduce the dosage. (2.2, 8.6)

FULL PRESCRIBING INFORMATION

1 INDICATIONS & USAGE

Famotidine tablets are indicated in adult and pediatric patients 40 kg and greater for the treatment of:

- active duodenal ulcer (DU).
- active gastric ulcer (GU).
- symptomatic nonerosive gastroesophageal reflux disease (GERD).
- erosive esophagitis due to GERD, diagnosed by biopsy.

Famotidine tablets are indicated in adults for the:

- treatment of pathological hypersecretory conditions (e.g., Zollinger-Ellison syndrome, multiple endocrine neoplasias).

- reduction of the risk of duodenal ulcer recurrence.

2 DOSAGE & ADMINISTRATION

2.1 Recommended Dosage

Table 1 shows the recommended dosage of famotidine 20 mg and 40 mg tablets in adult and pediatric patients weighing 40 kg and greater with normal renal function. The use of famotidine 20 mg and 40 mg tablets is not recommended in pediatric patients weighing less than 40 kg because the lowest available strength (20 mg) exceeds the recommended dose for these patients .Use another famotidine formulation for pediatric patients weighing less than 40 kg.

Table 1: Recommended Dosage and Duration of Famotidine Tablets in Adult and Pediatric Patients 40 kg and Greater with Normal Renal Function

Indication | Recommended Dosage | Recommended Duration
Active duodenal ulcer (DU) | 40 mg once daily; or 20 mg twice dailya | Up to 8 weeksb,c
Active gastric ulcer | 40 mg once daily | Up to 8 weeksc
Symptomatic nonerosive GERD | 20 mg twice daily | Up to 6 weeksc
Erosive esophagitis diagnosed by endoscopy | 20 mg twice daily; or 40 mg twice dailya | Up to 12 weeks
Pathological hypersecretory conditionsd | Starting dosage: 20 mg every 6 hours; adjust dosage to individual patient needs Maximum dosage 160 mg every 6 hours | As clinically indicated
Reduction of the risk of DU recurrenced | 20 mg once daily | 1 yearc or as clinically indicated

a Both dosages demonstrated effectiveness in clinical trials [see Clinical Studies (14)] .

b In clinical trials, the majority of patients healed within 4 weeks. For patients who do not heal after 4 weeks, consider an additional 2 to 4 weeks of treatment [see Clinical Studies (14.1)].

C Longer treatment durations have not been studied in clinical trials [see Clinical Studies (14.1, 14.2, 14.3)] .

d In pediatric patients, the safety and effectiveness of famotidine tablets have not been established for the reduction of the risk of duodenal ulcer recurrence or for treatment of pathological hypersecretory conditions [see Use in Specific Populations (8.4)] .

2.2 Dosage in Renal Impairment

Dosage adjustments of famotidine tablets are recommended for patients with moderate to severe renal impairment (creatinine clearance less than 60 mL/min) [see Use in Specific Populations (8.6)] . Table 2 shows the recommended maximum dosage of famotidine 20 mg or 40 mg tablets for patients with renal impairment, by indication. Use the lowest effective dose. Some dosage adjustments may require switching to other formulations of famotidine (e.g., oral suspension, lower dose tablet).

Table 2: Recommended Maximum Dosage of Famotidine Tablets in Adult and Pediatric Patients 40 kg and Greater with Moderate and Severe Renal Impairment

Indication | Recommended Maximum Dosages
Indication | Creatinine clearance 30 to 60 mL/minute | Creatinine clearance less than 30 mL/minute
Active duodenal ulcer (DU) | 20 mg once daily; or 40 mg every other day | 20 mg every other daya
Active gastric ulcer | 20 mg once daily; or 40 mg every other day | 20 mg every other daya
Symptomatic nonerosive GERD | 20 mg once daily | 20 mg every other daya
Erosive esophagitis diagnosed by endoscopyb | 20 mg once daily; or 40 mg every other dayb | 20 mg every other daya,b
Erosive esophagitis diagnosed by endoscopyb | 40 mg once dailyb | 20 mg once dailyb
Pathological hypersecretory conditionsc | Avoid used
Reduction of the risk of DU recurrencec | 20 mg every other daya | (see footnote)e

a An alternate dosage regimen is 10 mg once daily. Since 20 mg or 40 mg tablet strength cannot be used for this dosage regimen, use an alternate famotidine formulation.

b Dosage adjustments for renal impairment are provided for both dosing regimens (20 mg twice daily and 40 mg twice daily) which showed effectiveness for the treatment of erosive esophagitis in clinical trials [see Clinical Studies (14.4)] .

c In pediatric patients, the safety and effectiveness of famotidine tablets have not been established for the reduction of the risk of duodenal ulcer recurrence or for treatment of pathological hypersecretory conditions [see Use in Specific Populations (8.4)] .

d Doses required to treat pathological hypersecretory conditions may exceed the maximum doses evaluated in patients with impaired renal function. The risk for increased adverse reactions in renally impaired patients treated with famotidine tablets for pathological hypersecretory conditions is unknown.

e Recommended dosage regimen is 10 mg every other day. Since 20 mg or 40 mg tablet strength cannot be used for this dosage regimen, use an alternate famotidine formulation.

2.3 Administration Instructions

- Take famotidine tablets once daily before bedtime or twice daily in the morning and before bedtime, as recommended.
- Famotidine tablets may be taken with or without food [see Clinical Pharmacology (12.3)] .
- Famotidine tablets may be given with antacids.

3 DOSAGE FORMS & STRENGTHS

- 20 mg tablets: round, white to off-white film-coated tablets, debossed with “V” on one side and “15” on the other side.

4 CONTRAINDICATIONS

Famotidine tablets are contraindicated in patients with a history of serious hypersensitivity reactions (e.g., anaphylaxis) to famotidine or other histamine-2 (H2) receptor antagonists.

5 WARNINGS AND PRECAUTIONS

5.1 Central Nervous System Adverse Reactions

Central nervous system (CNS) adverse reactions, including confusion, delirium, hallucinations, disorientation, agitation, seizures, and lethargy, have been reported in elderly patients and patients with moderate and severe renal impairment treated with famotidine. Since famotidine blood levels are higher in patients with renal impairment than in patients with normal renal function, dosage adjustments are recommended in patients with renal impairment [see Dosage and Administration (2.2), Clinical Pharmacology (12.3)].

5.2 Concurrent Gastric Malignancy

In adults, symptomatic response to therapy with famotidine does not preclude the presence of gastric malignancy. Consider evaluation for gastric malignancy in adult patients who have a suboptimal response or an early symptomatic relapse after completing treatment with famotidine.

6 ADVERSE REACTIONS

6.1 Clinical Trial Experience

Because clinical trials are conducted under widely varying conditions, adverse reaction rates observed in the clinical trials of a drug cannot be directly compared to rates in the clinical trials of another drug and may not reflect the rates observed in practice.

Famotidine was studied in 7 US and international placebo- and active-controlled trials in approximately 2500 patients [see Clinical Studies (14)] . A total of 1442 patients were treated with famotidine, including 302 treated with 40 mg twice daily, 456 treated with 20 mg twice daily, 461 treated with 40 mg once daily, and 396 treated with 20 mg once daily. The population was 17-91 years old, fairly well distributed between gender and race; however, the predominant race treated was Caucasian.

The following adverse reactions occurred in greater than or equal to 1% of famotidine-treated patients: headache, dizziness and constipation.

The following other adverse reactions were reported in less than 1% of patients in clinical trials:

Body as a Whole:fever, asthenia, fatigue

Cardiovascular:palpitations

Gastrointestinal:elevated liver enzymes, vomiting, nausea, abdominal discomfort, anorexia, dry mouth

Hematologic:thrombocytopenia

Hypersensitivity:orbital edema, rash, conjunctival injection, bronchospasm

Musculoskeletal:musculoskeletal pain, arthralgia

Nervous System/Psychiatric:seizure, hallucinations, depression, anxiety, decreased libido, insomnia, somnolence

Skin:pruritus, dry skin, flushing

Special Senses:tinnitus, taste disorder

Other:impotence

6.2 Postmarketing Experience

The following adverse reactions have been identified during post-approval use of famotidine. Because these reactions are reported voluntarily from a population of uncertain size, it is not always possible to reliably estimate their frequency or establish a causal relationship to drug exposure.

Cardiovascular:arrhythmia, AV block, prolonged QT interval

Gastrointestinal:cholestatic jaundice, hepatitis

Hematologic:agranulocytosis, pancytopenia, leukopenia

Hypersensitivity:anaphylaxis, angioedema, facial edema, urticaria

Musculoskeletal:rhabdomyolysis, muscle cramps

Nervous System/Psychiatric:confusion, agitation, paresthesia

Respiratory:interstitial pneumonia

Skin:toxic epidermal necrolysis/Stevens-Johnson syndrome

7 DRUG INTERACTIONS

7.1 Drugs Dependent on Gastric pH for Absorption

Famotidine can reduce the absorption of other drugs, due to its effect on reducing intragastric acidity, leading to loss of efficacy of the concomitant drug.

Concomitant administration of famotidine with dasatinib, delavirdine mesylate, cefditoren, and fosamprenavir is not recommended.

See the prescribing information for other drugs dependent on gastric pH for absorption for administration instructions, including atazanavir, erlotinib, ketoconazole, itraconazole, ledipasvir/sofosbuvir, nilotinib, and rilpivirine.

7.2 Tizanidine (CYP1A2 Substrate)

Although not studied clinically, famotidine is considered a weak CYP1A2 inhibitor and may lead to substantial increases in blood concentrations of tizanidine, a CYP1A2 substrate. Avoid concomitant use with famotidine. If concomitant use is necessary, monitor for hypotension, bradycardia or excessive drowsiness. Refer to the full prescribing information for tizanidine.

8 USE IN SPECIFIC POPULATIONS

8.1 Pregnancy

Risk Summary

Available data with H2-receptor antagonists, including famotidine, in pregnant women are insufficient to establish a drug-associated risk of major birth defects, miscarriage or adverse maternal or fetal outcomes. In animal reproduction studies, no adverse development effects were observed with oral administration of famotidine at doses up to approximately 243 and 122 times, respectively, the recommended human dose of 80 mg per day for the treatment of erosive esophagitis (see Data).

The estimated background risk for major birth defects and miscarriage for the indicated population is unknown. All pregnancies have a background risk of birth defect, loss, or other adverse outcomes. In the U.S. general population, the background risk of major birth defects and miscarriage in clinically recognized pregnancies is 2 to 4% and 15 to 20%, respectively.

Data

Animal Data

Reproductive studies have been performed in rats and rabbits at oral doses of up to 2000 and 500 mg/kg/day, respectively, and in both species at intravenous doses of up to 200 mg/kg/day, and have revealed no significant evidence of impaired fertility or harm to the fetus due to famotidine. While no direct fetotoxic effects have been observed, sporadic abortions occurring only in mothers displaying marked decreased food intake were seen in some rabbits at oral doses of 200 mg/kg/day (about 49 times the recommended human dose of 80 mg per day, based on body surface area) or higher. There are, however, no adequate or well-controlled studies in pregnant women. Because animal reproductive studies are not always predictive of human response, this drug should be used during pregnancy only if clearly needed.

8.2 Lactation

Risk Summary

There are limited data available on the presence of famotidine in human breast milk. There were no effects on the breastfed infant. There are no data on famotidine effects on milk production. Famotidine is present in the milk of lactating rats (see Data).

The developmental and health benefits of breastfeeding should be considered along with the mother’s clinical need for famotidine and any potential adverse effects on the breastfed child from famotidine or from the underlying maternal condition.

Data

Animal Data

Transient growth depression was observed in young rats suckling from mothers treated with maternotoxic doses of famotidine at least 600 times the usual human dose.

8.4 Pediatric Use

The safety and effectiveness of famotidine have been established in pediatric patients for the treatment of peptic ulcer disease (i.e., duodenal ulcer, gastric ulcer) and GERD (i.e., symptomatic nonerosive GERD, erosive esophagitis as diagnosed by endoscopy). The use of famotidine and the recommended dosage of famotidine in these pediatric patients is supported by evidence from adequate and well-controlled studies of famotidine in adults and published pharmacokinetic and pharmacodynamic data in pediatric patients [see Dosage and Administration (2.1), Clinical Pharmacology (12.2, 12.3)] . In pediatric patients, the safety and effectiveness for the treatment of pathological hypersecretory conditions and reduction of risk of duodenal ulcer recurrence have not been established.

Famotidine 20 and 40 mg tablets are not recommended for use in pediatric patients weighing less than 40 kg because these tablet strengths exceed the recommended dose for these patients [see Dosage and Administration (2.1)] . For pediatric patients weighing less than 40 kg, consider another famotidine formulation (e.g., oral suspension, lower dose tablet).

8.5 Geriatric Use

Of the 1442 famotidine-treated patients in clinical studies, approximately 10% were 65 and older. In these studies, no overall differences in safety or effectiveness were observed between elderly and younger patients. In postmarketing experience, CNS adverse reactions have been reported in elderly patients with and without renal impairment receiving famotidine [see Warnings and Precautions (5.1)] .

Famotidine is known to be substantially excreted by the kidney, and the risk of adverse reactions to famotidine may be greater in elderly patients, particularly those with impaired renal function [see Use in Specific Populations (8.6)] .

In general, use the lowest effective dose of famotidine for an elderly patient and monitor renal function [see Dosage and Administration (2.2)].

8.6 Renal Impairment

CNS adverse reactions and prolonged QT intervals have been reported in patients with moderate and severe renal impairment [see Warnings and Precautions (5.1)]. The clearance of famotidine is reduced in adults with moderate and severe renal impairment compared to adults with normal renal function [see Clinical Pharmacology (12.3)]. No dosage adjustment is needed in patients with mild renal impairment (creatinine clearance greater than or equal to 60 mL/minute). Dosage reduction is recommended in adult and pediatric patients greater than or equal to 40 kg with moderate or severe renal impairment (creatinine clearance less than 60 mL/minute) [see Dosage and Administration (2.2)].

10 OVERDOSAGE

The types of adverse reactions in overdosage of famotidine are similar to the adverse reactions encountered with use of recommended dosages [see Adverse Reactions (6.1)] .

In the event of overdosage, treatment should be symptomatic and supportive. Unabsorbed material should be removed from the gastrointestinal tract, the patient should be monitored, and supportive therapy should be employed.

Due to low binding to plasma proteins, famotidine is eliminated by hemodialysis. There is limited experience on the usefulness of hemodialysis as a treatment for famotidine overdosage.

11 DESCRIPTION

The active ingredient in famotidine tablets is a histamine-2 (H2) receptor antagonist. Famotidine is

N'-(aminosulfonyl)-3-[[[2-[(diaminomethylene)amino]-4-thiazolyl]methyl]thio]propanimidamide. The empirical formula of famotidine is C8H15N7O2S3and its molecular weight is 337.43. Its structural formula is:

Each famotidine tablet for oral administration contains either 20 mg or 40 mg of famotidine and the following inactive ingredients: hydroxypropyl cellulose, magnesium stearate, microcrystalline cellulose, pregelatinized starch, sodium starch glycolate (type-A), hypromellose, titanium dioxide, triacetin, talc and macrogol.

Famotidine is a white to pale yellow crystalline compound that is freely soluble in glacial acetic acid, slightly soluble in methanol, very slightly soluble in water, and practically insoluble in ethanol.

12 CLINICAL PHARMACOLOGY

12.1 Mechanism of Action

Famotidine is a competitive inhibitor of histamine-2 (H2) receptors. The primary clinically important pharmacologic activity of famotidine is inhibition of gastric secretion. Both the acid concentration and volume of gastric secretion are suppressed by famotidine, while changes in pepsin secretion are proportional to volume output.

12.2 Pharmacodynamics

Adults

Famotidine inhibited both basal and nocturnal gastric secretion, as well as secretion stimulated by food and pentagastrin. After oral administration of famotidine, the onset of the antisecretory effect occurred within one hour; the maximum effect was dose-dependent, occurring within one to three hours. Duration of inhibition of secretion by doses of 20 mg and 40 mg was 10 to 12 hours.

Single evening oral doses of 20 mg and 40 mg inhibited basal and nocturnal acid secretion in all subjects; mean nocturnal gastric acid secretion was inhibited by 86% and 94%, respectively, for a period of at least 10 hours. The same doses given in the morning suppressed food-stimulated acid secretion in all subjects. The mean suppression was 76% and 84%, respectively, 3 to 5 hours after administration, and 25% and 30%, respectively, 8 to 10 hours after administration. In some subjects who received the 20 mg dose, however, the antisecretory effect was dissipated within 6 to 8 hours. There was no cumulative effect with repeated doses. The nocturnal intragastric pH was raised by evening doses of 20 mg and 40 mg of famotidine to mean values of 5.0 and 6.4, respectively. When famotidine was given after breakfast, the basal daytime interdigestive pH at 3 and 8 hours after 20 mg or 40 mg of famotidine was raised to about 5.

Famotidine had little or no effect on fasting or postprandial serum gastrin levels. Gastric emptying and exocrine pancreatic function were not affected by famotidine.

In clinical pharmacology studies, systemic effects of famotidine in the CNS, cardiovascular, respiratory or endocrine systems were not noted. Also, no anti-androgenic effects were noted. Serum hormone levels, including prolactin, cortisol, thyroxine (T4), and testosterone, were not altered after treatment with famotidine.

Pediatric Patients

Pharmacodynamics of famotidine, assessed by gastric pH, were evaluated in 5 pediatric patients 2 to 13 years of age using the sigmoid Emaxmodel. These data suggest that the relationship between serum concentration of famotidine and gastric acid suppression is similar to that observed in adults (see Table 3).

Table 3: Serum Concentrations of Famotidine Associated with Gastric Acid Reduction in Famotidine-Treated Pediatric and Adult Patientsa

 | EC50(ng/mL) a
Pediatric Patients | 26 ± 13
Adults
Healthy adult subjects | 26.5 ± 10.3
Adult patients with upper GI bleeding | 18.7 ± 10.8

a Using the Sigmoid Emax model, serum concentrations of famotidine associated with 50% maximum gastric acid reduction are presented as means ± SD.

In a study examining the effect of famotidine on gastric pH and duration of acid suppression in pediatric patients, four pediatric patients ages 11 to 15 years of age using the oral formulation at a dose of 0.5 mg/kg, maintained a gastric pH above 5 for 13.5 ± 1.8 hours.

12.3 Pharmacokinetics

Absorption

Famotidine is incompletely absorbed. The bioavailability of oral doses is 40 to 45%. Bioavailability may be slightly increased by food, or slightly decreased by antacids; however, these effects are of no clinical consequence.

Peak famotidine plasma levels occur in 1 to 3 hours. Plasma levels after multiple dosages are similar to those after single doses.

Distribution

Fifteen to 20% of famotidine in plasma is protein bound.

Elimination

Metabolism

Famotidine undergoes minimal first-pass metabolism. Twenty-five to 30% of an oral dose was recovered in the urine as unchanged compound. The only metabolite identified in humans is the S-oxide.

Excretion

Famotidine has an elimination half-life of 2.5-3.5 hours. Famotidine is eliminated by renal (65 to 70%) and metabolic (30 to 35%) routes. Renal clearance is 250 to 450 mL/minute, indicating some tubular excretion.

Specific Populations

Pediatric Patients

Bioavailability studies of 8 pediatric patients (11 to 15 years of age) showed a mean oral bioavailability of 0.5 compared to adult values of 0.42 to 0.49. Oral doses of 0.5 mg per kg achieved AUCs of 580 ± 60 ng•hr/mL in pediatric patients 11 to 15 years of age, compared to 482 ± 181 ng•hr/mL in adults treated with 40 mg orally.

Patients with Renal Impairment

In adult patients with severe renal impairment (creatinine clearance less than 30 mL/minute), the systemic exposure (AUC) of famotidine increased at least 5-fold. In patients with moderate renal impairment (creatinine clearance between 30 to 60 mL/minute), the AUC of famotidine increased at least 2-fold [see Dosage and Administration (2.2), Use in Specific Population (8.6)] .

Drug Interaction Studies

Human Organic Anion Transporter (OAT) 1 and 3: In vitrostudies indicate that famotidine is a substrate for OAT1 and OAT3. Following coadministration of probenecid (1500 mg), an inhibitor of OAT1 and OAT3, with a single oral 20 mg dose of famotidine in 8 healthy subjects, the serum AUC0-10hof famotidine increased from 424 to 768 ng•hr/mL and the maximum serum concentration (Cmax) increased from 73 to 113 ng/mL. Renal clearance, urinary excretion rate and amount of famotidine excreted unchanged in urine were decreased. The clinical relevance of this interaction is unknown.

Multidrug and Toxin Extrusion Protein 1 (MATE-1):An in vitrostudy showed that famotidine is an inhibitor of MATE-1. However, no clinically significant interaction with metformin, a substrate for MATE-1, was observed.

CYP1A2:Famotidine is a weak CYP1A2 inhibitor.

13 NONCLINICAL TOXICOLOGY

13.1 Carcinogenesis & Mutagenesis & Impairment of Fertility

Carcinogenic potential of famotidine was assessed in a 106-week oral carcinogenicity study in rats and a 92-week oral carcinogenicity study in mice. In the 106-week study in rats and the 92-week study in mice at oral doses of up to 2000 mg/kg/day (approximately 243 and 122 times, respectively, based on body surface area, the recommended human dose of 80 mg per day for the treatment of erosive esophagitis), there was no evidence of carcinogenic potential for famotidine.

Famotidine was negative in the microbial mutagen test (Ames test) using Salmonella typhimuriumand Escherichia coliwith or without rat liver enzyme activation at concentrations up to 10,000 mcg/plate. In in vivostudies in mice, with a micronucleus test and a chromosomal aberration test, no evidence of a mutagenic effect was observed.

In studies with rats given oral doses of up to 2000 mg/kg/day (approximately 243 times, based on body surface area, the recommended human dose of 80 mg per day) fertility and reproductive performance were not affected.

14 CLINICAL STUDIES

14.1 Active Duodenal Ulcer

In a U.S. multicenter, double-blind trial in adult outpatients with endoscopically confirmed duodenal ulcer (DU), orally administered famotidine was compared to placebo. As shown in Table 4, 70% of patients treated with famotidine 40 mg at bedtime were healed by Week 4. Most patients’ DU healed within 4 weeks.

Patients not healed by Week 4 were continued in the trial. By Week 8, 83% of patients treated with famotidine had healed DU, compared to 45% of patients treated with placebo. The incidence of DU healing with famotidine was greater than with placebo at each time point based on proportion of endoscopically confirmed healed DUs. Trials have not assessed the safety of famotidine in uncomplicated active DU for periods of more than 8 weeks.

Table 4: Patients with Endoscopically Confirmed Healed Duodenal Ulcers

 | Famotidine 40 mg at bedtime (N=89) | Famotidine 20 mg twice daily (N=84) | Placebo at bedtime (N=97)
Week 2 | 32%a | 38%a | 17%
Week 4 | 70%a | 67%a | 31%

ap<0.001 vs. placebo

In this study, time to relief of daytime and nocturnal pain was shorter for patients receiving famotidine than for patients receiving placebo; patients receiving famotidine also took less antacid than patients receiving placebo.

14.2 Active Gastric Ulcer

In both a U.S. and an international multicenter, double-blind trials in patients with endoscopically confirmed active gastric ulcer (GU), orally administered famotidine 40 mg at bedtime was compared to placebo. Antacids were permitted during the trials, but consumption was not significantly different between the famotidine and placebo groups.

As shown in Table 5, the incidence of GU healing confirmed by endoscopy (dropouts counted as unhealed) with famotidine was greater than placebo at Weeks 6 and 8 in the U.S. trial, and at Weeks 4, 6 and 8 in the international trial. In these trials, most famotidine-treated patients healed within 6 weeks. Trials have not assessed the safety of famotidine in uncomplicated active GU for periods of more than 8 weeks.

Table 5: Patients with Endoscopically Confirmed Healed Gastric Ulcers

 | U.S. Study (N=149) |  | International Study (N=294)
 | Famotidine 40 mg at bedtime (N=74) | Placebo at bedtime (N=75) | Famotidine 40 mg at bedtime (N=149) | Placebo at bedtime (N=145)
Week 4 | 45% | 39% | 47%a | 31%
Week 6 | 66%a | 44% | 65%a | 46%
Week 8 | 78%b | 64% | 80%a | 54%

ap≤0.01 vs. placebo

bp≤0.05 vs. placebo

Time to complete relief of daytime and nighttime pain was statistically significantly shorter for patients receiving famotidine than for patients receiving placebo; however, neither trial demonstrated a statistically significant difference in the proportion of patients whose pain was relieved by the end of the trial (Week 8).

14.3 Symptomatic Gastroesophageal Reflux Disease (GERD)

Orally administered famotidine was compared to placebo in a U.S. trial that enrolled patients with symptoms of GERD and without endoscopic evidence of esophageal erosion or ulceration. As shown in Table 6, patients treated with famotidine 20 mg twice daily had greater improvement in symptomatic GERD than patients treated with 40 mg at bedtime or placebo.

Table 6: Patients with Improvement of Symptomatic GERD (N=376)

 | Famotidine 20 mg twice daily (N=154) | Famotidine 40 mg at bedtime (N=149) | Placebo at bedtime (N=73)
Week 6 | 82%a | 69% | 62%

a p≤0.01 vs. placebo

14.4 Erosive Esophagitis due to GERD

Healing of endoscopically verified erosion and symptomatic improvement were studied in a U.S. and an international double-blind trials. Healing was defined as complete resolution of all erosions visible with endoscopy. The U.S. trial comparing orally administered famotidine 40 mg twice daily to placebo and orally administered famotidine 20 mg twice daily showed a significantly greater percentage of healing of erosive esophagitis for famotidine 40 mg twice daily at Weeks 6 and 12 (Table 7).

Table 7: Patients with Endoscopic Healing of Erosive Esophagitis - U.S. Study (N=318)

 | Famotidine 40 mg twice daily (N=127) | Famotidine 20 mg twice daily (N=125) | Placebo twice daily (N=66)
Week 6 | 48%a,b | 32% | 18%
Week 12 | 69%a,c | 54%a | 29%

ap≤0.01 vs. placebo

bp≤0.01 vs. famotidine 20 mg twice daily

cp≤0.05 vs. famotidine 20 mg twice daily

As compared to placebo, patients in the U.S. trial who received famotidine had faster relief of daytime and nighttime heartburn, and a greater percentage of famotidine-treated patients experienced complete relief of nighttime heartburn. These differences were statistically significant.

In the international trial, when orally administered famotidine 40 mg twice daily was compared to orally administered ranitidine 150 mg twice daily, a statistically significantly greater percentage of healing of erosive esophagitis was observed with famotidine 40 mg twice daily at Week 12 (Table 8). There was, however, no significant difference in symptom relief among treatment groups.

Table 8: Patients with Endoscopic Healing of Erosive Esophagitis - International Study (N=440)

 | Famotidine 40 mg twice daily (N=175) | Famotidine 20 mg twice daily (N=93) | Ranitidine 150 mg twice daily (N=172)
Week 6 | 48% | 52% | 42%
Week 12 | 71%a | 68% | 60%

ap≤0.05 vs ranitidine 150 mg twice daily

14.5 Pathological Hypersecretory Conditions

In trials of patients with pathological hypersecretory conditions such as Zollinger-Ellison syndrome with or without multiple endocrine neoplasias, famotidine significantly inhibited gastric acid secretion and controlled associated symptoms. Orally administered famotidine dosages from 20 mg to 160 mg every 6 hours maintained basal acid secretion below 10 mEq/hour; initial dosages were titrated to the individual patient need and subsequent adjustments were necessary with time in some patients.

14.6 Risk Reduction of Duodenal Ulcer Recurrence

Two randomized, double-blind, multicenter trials in patients with endoscopically confirmed healed DUs demonstrated that patients receiving treatment with orally administered famotidine 20 mg at bedtime had lower rates of DU recurrence, as compared with placebo.

- In the U.S. trial, DU recurrence within 12 months was 2.4 times greater in patients treated with placebo than in the patients treated with famotidine. The 89 famotidine-treated patients had a cumulative observed DU recurrence rate of 23%, compared to a 57% in the 89 patients receiving placebo (p<0.01).
- In the international trial, the cumulative observed DU recurrence within 12 months in the 307 famotidine-treated patients was 36%, compared to 76% in the 325 patients who received placebo (p<0.01).

Controlled trials have not extended beyond one year.

16 HOW SUPPLIED/STORAGE AND HANDLING

Famotidine tablets are supplied as follows:

20 mg, round, white to off-white film-coated tablets, debossed with “V” on one side and “15” on the other side.

NDC: 70518-4574-00

PACKAGING: 10 in 1 BOTTLE PLASTIC

Storage

Store at 25°C (77°F); excursions permitted to 15-30°C (59-86°F) (See USP Controlled Room Temperature). Dispense in a USP tight, light-resistant container.

Repackaged and Distributed By:

Remedy Repack, Inc.

625 Kolter Dr. Suite #4 Indiana, PA 1-724-465-8762

17 PATIENT COUNSELING INFORMATION

Central Nervous System (CNS) Adverse Reactions

Advise elderly patients and those with moderate and severe renal impairment of the risk of CNS adverse reactions, including confusion, delirium, hallucinations, disorientation, agitation, seizures, and lethargy [see Warnings and Precautions (5.1)] . Report symptoms immediately to a healthcare provider.

QT Prolongation

Advise patients with moderate and severe renal impairment of the risk of QT interval prolongation [see Use in Specific Populations (8.6)] . Report new cardiac symptoms, such as palpitations, fainting and dizziness or lightheadedness immediately to a healthcare provider.

Administration

Advise patients:

- Take famotidine tablets once daily before bedtime or twice daily in the morning and before bedtime, as recommended.
- Famotidine tablets may be taken with or without food.
- Famotidine tablets may be given with antacids.

Repackaged By / Distributed By: RemedyRepack Inc.

625 Kolter Drive, Indiana, PA 15701

(724) 465-8762

PACKAGE LABEL

DRUG: FAMOTIDINE

GENERIC: FAMOTIDINE

DOSAGE: TABLET, FILM COATED

ADMINSTRATION: ORAL

NDC: 70518-4574-0

COLOR: white

SHAPE: ROUND

SCORE: No score

SIZE: 6 mm

PACKAGING: 10 in 1 BOTTLE, PLASTIC

ACTIVE INGREDIENT(S):

- FAMOTIDINE 20mg in 1

INACTIVE INGREDIENT(S):

- HYDROXYPROPYL CELLULOSE, UNSPECIFIED
- MAGNESIUM STEARATE
- MICROCRYSTALLINE CELLULOSE
- SODIUM STARCH GLYCOLATE TYPE A
- TITANIUM DIOXIDE
- TRIACETIN
- POLYETHYLENE GLYCOL, UNSPECIFIED
- STARCH, CORN
- HYPROMELLOSE, UNSPECIFIED